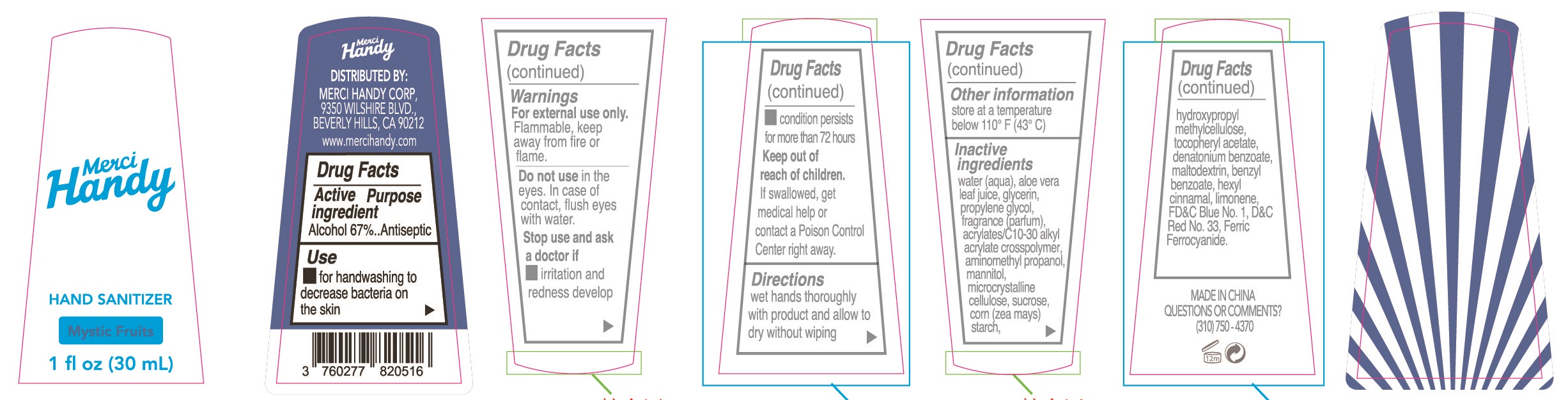 DRUG LABEL: Hand Sanitizer
NDC: 43473-104 | Form: GEL
Manufacturer: Nantong Health & Beyond Hygienic Products Inc.
Category: otc | Type: HUMAN OTC DRUG LABEL
Date: 20190319

ACTIVE INGREDIENTS: ALCOHOL 67 mL/100 mL
INACTIVE INGREDIENTS: D&C RED NO. 33; FD&C BLUE NO. 1; LIMONENE, (+)-; BENZYL BENZOATE; FERRIC FERROCYANIDE; DENATONIUM BENZOATE; MALTODEXTRIN; .ALPHA.-HEXYLCINNAMALDEHYDE; PROPYLENE GLYCOL; MANNITOL; WATER; ALOE VERA LEAF; GLYCERIN; CARBOMER INTERPOLYMER TYPE A (55000 CPS); AMINOMETHYLPROPANOL; CELLULOSE, MICROCRYSTALLINE; SUCROSE; STARCH, CORN; .ALPHA.-TOCOPHEROL ACETATE; HYPROMELLOSES

Active ingredient
Alcohol 67%

Purpose
Antiseptic

Uses

for handwashing to decrease bacteria on the skin.

Warnings

For external use only. Flammable, keep away from fire or flame.

Do not use in the eyes.In case of contact, flush eyes with water.

Stop use and ask a doctor if

- irritation and redness develop.
- condition persists for more than 72 hours

Keep out of reach of children. If swallowed, get medical help or contact a Poison Control Center right away.

Directions

wet hand thoroughly with product and allow to dry without wiping

Other information

store at a temperature below 110 F(43 C)

Inactive ingredients

water(aqua), aloe vera leaf juice, glycerin, propylene glycol, fragrance(parfum), acrylates/C30-10 alkyl acrylate crosspolymer, aminomethyl propanol, mannitol, microcrystalline cellulose, sucrose, corn(zea mays) starch, hydroxpropyl methyl cellulose, tocopheryl acetate, denatonium benzonate, maltodextrin, benzyl benzoate, hexyl cinnamal, limonene, FD&C Blue No.1, D&C Red No.33, Ferric Ferrocyanide.